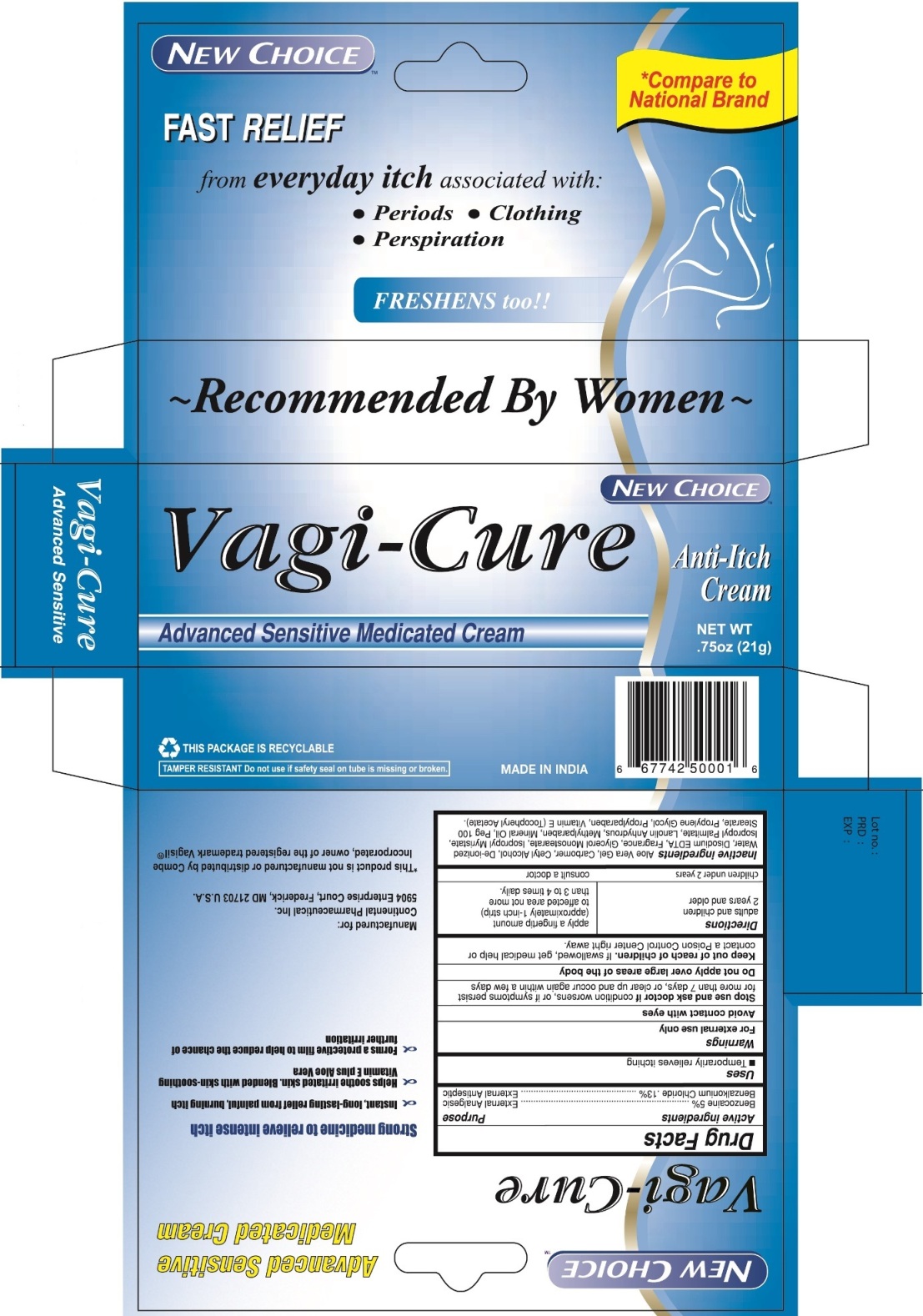 DRUG LABEL: Vagi-Cure Advanced Sensitive Medicated
NDC: 76466-011 | Form: CREAM
Manufacturer: SCI International, Inc. DBA Continental Pharmaceuticals
Category: otc | Type: HUMAN OTC DRUG LABEL
Date: 20220224

ACTIVE INGREDIENTS: BENZOCAINE 5 g/100 g; BENZALKONIUM CHLORIDE 0.13 g/100 g
INACTIVE INGREDIENTS: ALOE VERA LEAF; CARBOXYPOLYMETHYLENE; CETYL ALCOHOL; WATER; EDETATE DISODIUM; GLYCERYL MONOSTEARATE; ISOPROPYL MYRISTATE; ISOPROPYL PALMITATE; LANOLIN; METHYLPARABEN; MINERAL OIL; PEG-100 STEARATE; PROPYLENE GLYCOL; PROPYLPARABEN; .ALPHA.-TOCOPHEROL ACETATE

Vagi-Cure Advanced Sensitive Medicated

Active ingredients

Benzocaine 5%

Benzalkonium Chloride .13%

Purpose

External Analgesic

External Antiseptic

Uses

- Temporarily relieves itching

Warnings

For external use only

Avoid contact with eyes

Stop use and ask doctor if condition worsens, or if symptoms persist for more than 7 days or clear up and occur again within a few days.

Do not apply over large areas of the body

Keep out of reach of children. If swallowed, get medical help or contact a Poison Control Center right away.

Directions

adult and children 2 years and older

apply a fingertip amount (approximately 1-inch strip) to affected area not more than 3 to 4 times daily.

children under 2 years

consult a doctor

Inactive ingredients

Aloe Vera Gel, Carbomer, Cetyl Alcohol, De-ionized Water, Disodium EDTA, Fragrance, Glycerol Monostearate, Isopropyl Myristate, Isopropyl Palmitate, Lanolin Anhydrous, Methylparaben, Mineral Oil, Peg 100 Stearate, Propylene Glycol, Propylparaben, Vitamin E (Tocopheryl Acetate).

PACKAGE LABEL

PRINCIPAL DISPLAY PANEL

Vagi-Cure

Anti-Itch Cream

Advance Sensitive Medicated Cream

NET WT 0.75oz (21g)